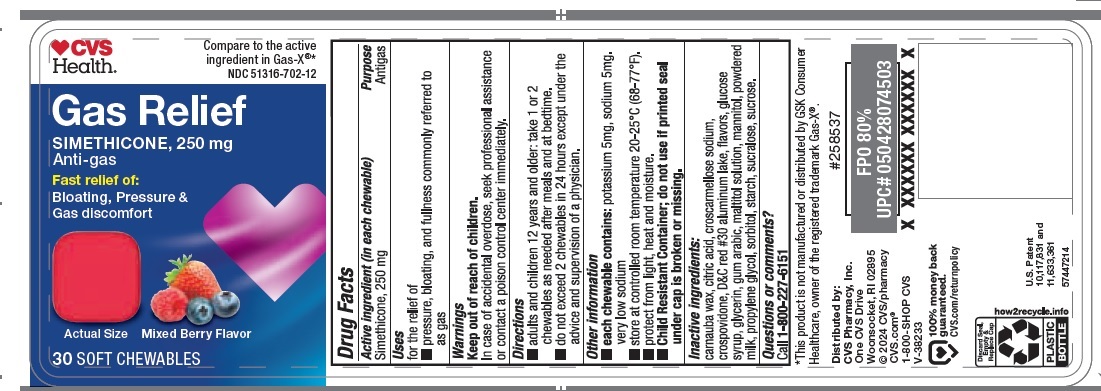 DRUG LABEL: Gas Relief SIMETHICONE 250 mg Anti-gas
NDC: 51316-702 | Form: TABLET, CHEWABLE
Manufacturer: CVS Pharmacy, Inc.
Category: otc | Type: HUMAN OTC DRUG LABEL
Date: 20250206

ACTIVE INGREDIENTS: DIMETHICONE 250 mg/1 1
INACTIVE INGREDIENTS: MANNITOL; MILK PROTEIN CONCENTRATE; PROPYLENE GLYCOL; SORBITOL; STARCH, CORN; SUCRALOSE; SUCROSE; CARNAUBA WAX; MALTITOL; ANHYDROUS CITRIC ACID; CROSCARMELLOSE SODIUM; CROSPOVIDONE; D&C RED NO. 30 ALUMINUM LAKE; CORN SYRUP; GLYCERIN; ACACIA

Gas Relief SIMETHICONE, 250 mg Anti-gas

Active ingredient (in each chewable)

Simethicone, 250 mg

Purpose

Antigas

Uses

for the relief of

- pressure, bloating, and fullness commonly referred to as gas

Warnings

Keep out of reach of children.

In case of accidental overdose, seek professional assistance or contact a poison control center immediately.

Directions

- adults and children 12 years and older: take 1 or 2 chewables as needed after meals and at bedtime.
- do not exceed 2 chewables in 24 hours except under the advice and supervision of a physician.

Other information

- each chewable contains: potassium 5 mg, sodium 5 mg.

very low sodium

- store at controlled room temperature 20-25°C (68-77°F).
- protect from light, heat and moisture.
- Child Resistant Container; do not use if printed seal under cap is broken or missing.

Inactive ingredients:

carnauba wax, citric acid, croscarmellose sodium, crospovidone, D&C red #30 aluminum lake, flavors, glucose syrup, glycerin, gum arabic, maltitol solution,mannitol, powdered milk, propylene glycol, sorbitol, starch, sucralose, sucrose.

Questions or comments?

Call 1-800-227-6151

Principal display Panel-250 mg label

CVS Health Compare to the active ingredient in Gas-X®*

NDC 51316-702-12

Gas Relief

SIMETHICONE, 250 mg

Anti-gas

Fast Relief of:

Bloating, Pressure &
Gas discomfort

Actual Size Mixed Berry Flavor

30 SOFT CHEWABLES